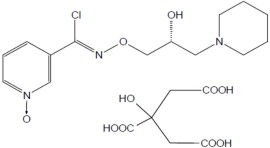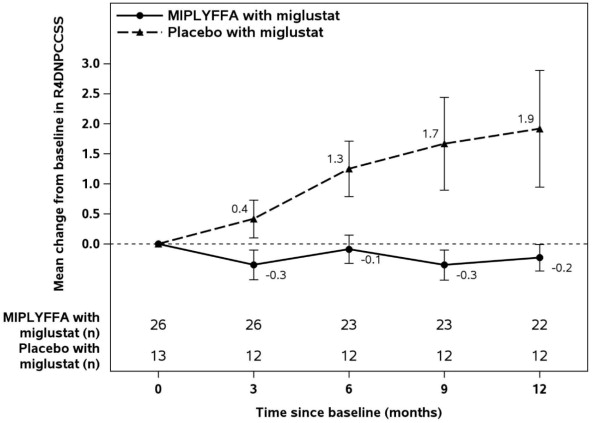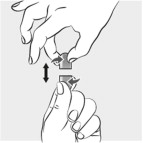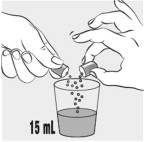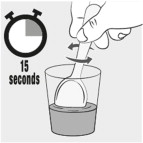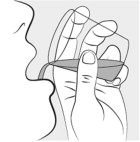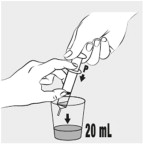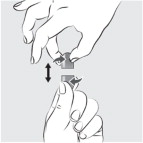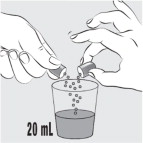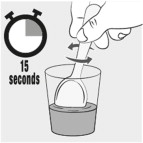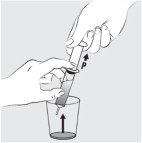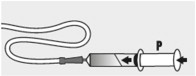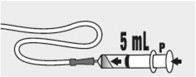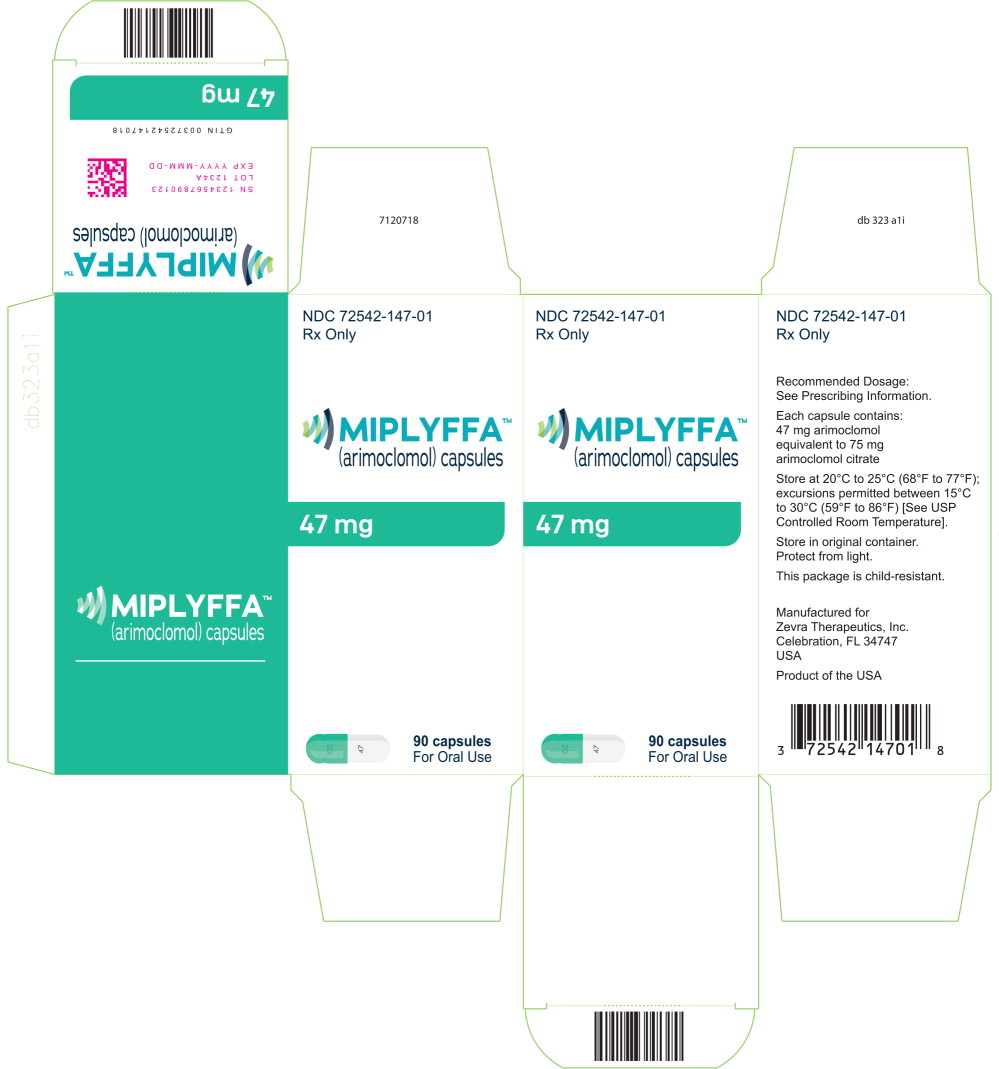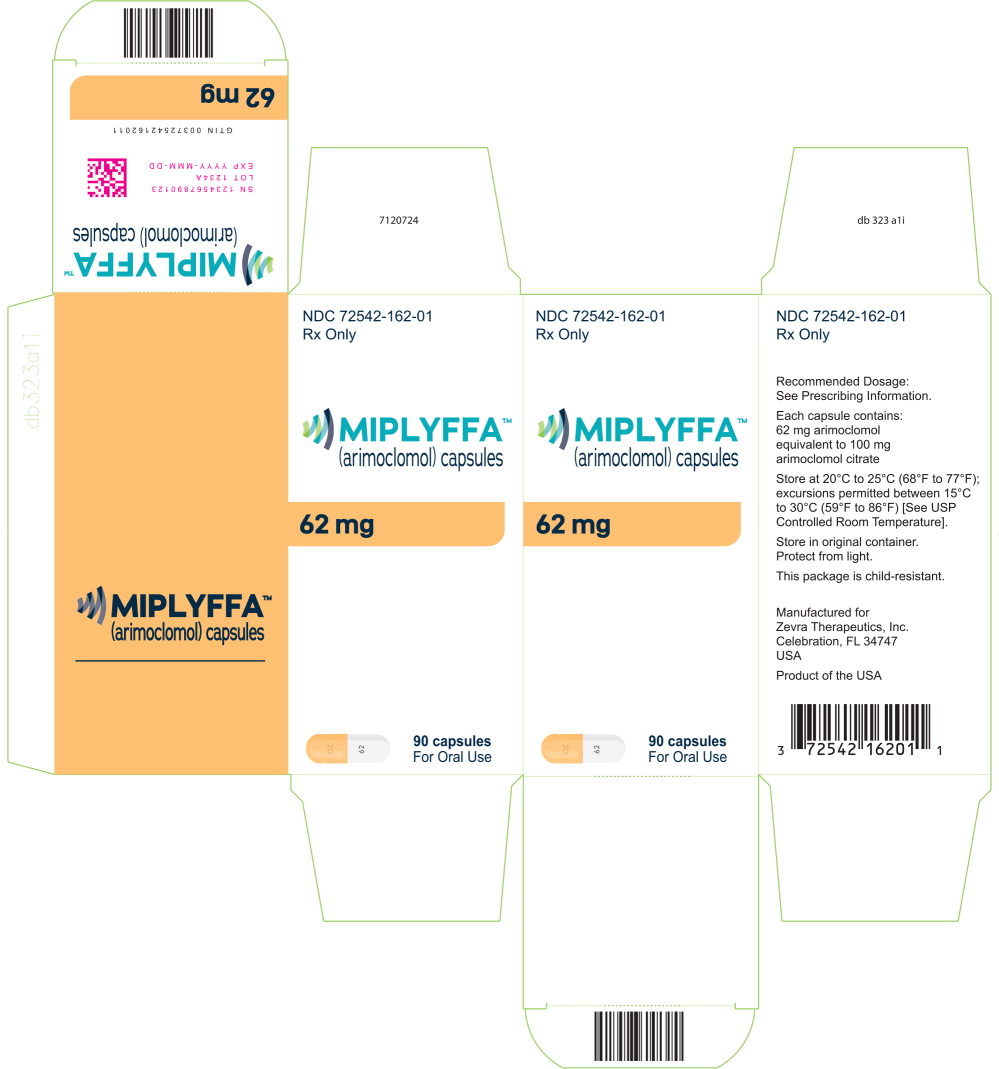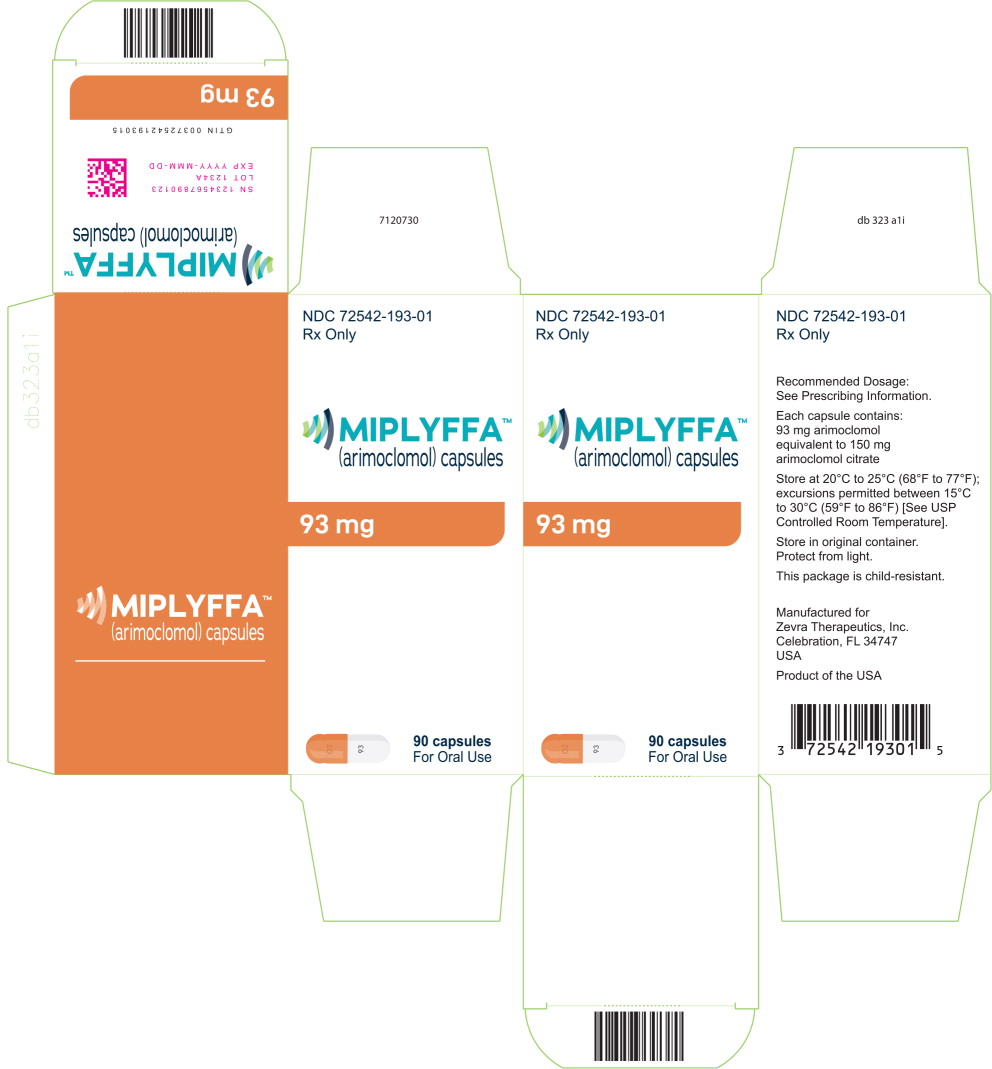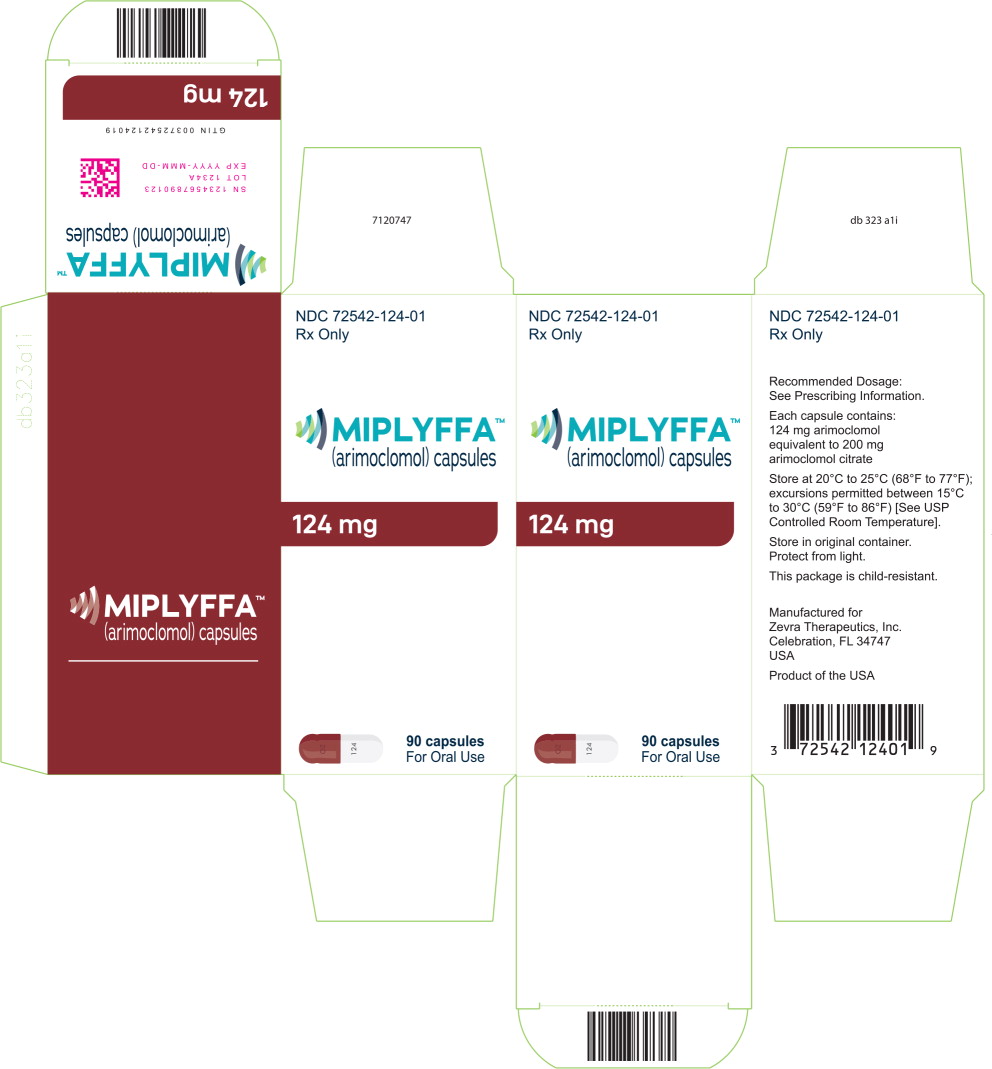 DRUG LABEL: MIPLYFFA
NDC: 72542-147 | Form: CAPSULE
Manufacturer: Acer Therapeutics Inc.
Category: prescription | Type: HUMAN PRESCRIPTION DRUG LABEL
Date: 20241002

ACTIVE INGREDIENTS: ARIMOCLOMOL CITRATE 47 mg/1 1
INACTIVE INGREDIENTS: MICROCRYSTALLINE CELLULOSE; MAGNESIUM STEARATE

HIGHLIGHTS OF PRESCRIBING INFORMATION

These highlights do not include all the information needed to use MIPLYFFA™safely and effectively. See full prescribing information for MIPLYFFA.
MIPLYFFA (arimoclomol) capsules, for oral use
Initial U.S. Approval: 2024

1 INDICATIONS AND USAGE

MIPLYFFA is indicated for use in combination with miglustat for the treatment of neurological manifestations of Niemann-Pick disease type C (NPC) in adult and pediatric patients 2 years of age and older. (1)

2 DOSAGE AND ADMINISTRATION

- Recommended MIPLYFFA oral dosage, in combination with miglustat, for patients with actual body weight of (2.1):
  - 8 kg to 15 kg, is 47 mg three times a day
  - > 15 kg to 30 kg, is 62 mg three times a day
  - > 30 kg to 55 kg, is 93 mg three times a day
  - > 55 kg, is 124 mg three times a day
- Administer with or without food. (2.1)
- See full prescribing information for recommended dosage in patients with an eGFR ≥ 15 to < 50 mL/minute. (2.2)
- See full prescribing information for instructions on preparation and administration. (2.3)

3 DOSAGE FORMS AND STRENGTHS

- Capsules: 47 mg, 62 mg, 93 mg and 124 mg of arimoclomol. (3)

4 CONTRAINDICATIONS

None. (4)

5 WARNINGS AND PRECAUTIONS

- Hypersensitivity Reactions: Urticaria and angioedema have been reported. Discontinue MIPLYFFA in patients who develop these adverse reactions. (5.1)
- Embryofetal Toxicity: May cause fetal harm. Advise pregnant females of the potential risk to the fetus and consider pregnancy planning and prevention. (5.2)
- Increased Creatinine without Affecting Glomerular Function:Mean increases in serum creatinine of 10-20% have been reported. Use alternative measures to assess renal function which are not based on creatinine. (5.3)

6 ADVERSE REACTIONS

Most common adverse reactions (≥15%) are: Upper respiratory tract infection, diarrhea, and decreased weight. (6.1)

To report SUSPECTED ADVERSE REACTIONS, contact Zevra Therapeutics, Inc. at toll-free phone 1-844-600-2237 or FDA at 1-800-FDA-1088 orwww.fda.gov/medwatch.

7 DRUG INTERACTIONS

- Substrates of the Organic Cationic Transporter 2 (OCT2 substrates): Monitor for adverse reactions and reduce the dosage of the OCT2 substrate. (7.1)

8 USE IN SPECIFIC POPULATIONS

- Females and Males of Reproductive Potential:Based on animal findings, MIPLYFFA may impair fertility. (8.3)

FULL PRESCRIBING INFORMATION

1 INDICATIONS AND USAGE

MIPLYFFA is indicated for use in combination with miglustat for the treatment of neurological manifestations of Niemann-Pick disease type C (NPC) in adult and pediatric patients 2 years of age and older.

2 DOSAGE AND ADMINISTRATION

2.1 Recommended Dosage

The recommended oral dosage of MIPLYFFA, in combination with miglustat, for patients with an actual body weight of:

- 8 kg to 15 kg, is 47 mg three times a day
- > 15 kg to 30 kg, is 62 mg three times a day
- > 30 kg to 55 kg, is 93 mg three times a day
- > 55 kg, is 124 mg three times a day

Administer MIPLYFFA with or without food.

Missed Dose

If a dose of MIPLYFFA is missed, advise the patient to skip the missed dose and to resume taking the prescribed dose at the next scheduled time.

2.2 Recommended Dosage in Patients with Renal Impairment

The recommended dosage of MIPLYFFA, in combination with miglustat, in patients with an eGFR ≥ 50 mL/minute is the same as the recommended dosage in patients with normal renal function [see Dosage and Administration (2.1)].

For patients with an eGFR ≥ 15 to < 50 mL/minute, the recommended oral dosage of MIPLYFFA, in combination with miglustat, for patients with an actual body weight of [see Use in Specific Populations (8.6) and Clinical Pharmacology (12.3)] :

- 8 kg to 15 kg, is 47 mg two times a day
- > 15 kg to 30 kg, is 62 mg two times a day
- > 30 kg to 55 kg, is 93 mg two times a day
- > 55 kg, is 124 mg two times a day

Administer MIPLYFFA with or without food.

2.3 Preparation and Administration Instructions

Swallow MIPLYFFA whole. However, for patients who have difficulty swallowing capsules, administer MIPLYFFA in one of two ways:

Oral Administration

1. Carefully open the capsule and sprinkle the entire contents into 15 mL of water or apple juice or 15 mL of soft food (e.g., applesauce, pudding, or yogurt).
2. Stir the mixture for 15 seconds.
3. Consume the entire mixture immediately.

Feeding Tube Administration (nasogastric or gastric tube)

1. Carefully open the capsule and sprinkle the entire contents into 20 mL of water. Do not add the capsule contents to other liquids besides water.
2. Stir the mixture for 15 seconds.
3. Administer the entire mixture immediately via feeding tube.
4. Flush the feeding tube with 5 mL of water after administration.

Do not save the mixture for later use.

3 DOSAGE FORMS AND STRENGTHS

MIPLYFFA (arimoclomol) capsules are available as follows:

MIPLYFFA Strength | Description of Capsules
47 mg | White opaque body with black printing “47”, and green opaque cap with black printing “OZ”
62 mg | White opaque body with black printing “62”, and yellow opaque cap with black printing “OZ”
93 mg | White opaque body with black printing “93”, and orange opaque cap with black printing “OZ”
124 mg | White opaque body with black printing “124”, and red opaque cap with black printing “OZ”

4 CONTRAINDICATIONS

None.

5 WARNINGS AND PRECAUTIONS

5.1 Hypersensitivity Reactions

Hypersensitivity reactions such as urticaria and angioedema have been reported in patients treated with MIPLYFFA during Trial 1 [see Clinical Studies (14)] : two patients reported both urticaria and angioedema (6%) and one patient (3%) experienced urticaria alone. The reactions occurred within the first two months of treatment. Discontinue MIPLYFFA in patients who develop severe hypersensitivity reactions. If a mild or moderate hypersensitivity reaction occurs, stop MIPLYFFA and treat promptly. Monitor the patient until signs and symptoms resolve [see Adverse Reactions (6.1)].

5.2 Embryofetal Toxicity

Based on findings from animal reproduction studies, MIPLYFFA may cause embryofetal harm when administered during pregnancy. In animal reproduction studies, oral administration of arimoclomol to pregnant rats and rabbits resulted in post-implantation loss and structural abnormalities in offspring. These occurred at exposures equal to or greater than 10- and 5-fold, for rats and rabbits respectively, the human exposure at the maximum recommended human daily dose of 372 mg. Advise pregnant females of the potential risk to the fetus. Consider pregnancy planning and prevention for females of reproductive potential [see Use in Specific Populations (8.1, 8.3)] .

5.3 Increased Creatinine without Affecting Glomerular Function

Across clinical trials of MIPLYFFA consisting of patients with NPC, healthy subjects, and patients with other diseases, there were mean increases in serum creatinine of 10% to 20% compared to baseline. These increases occurred mostly in the first month of MIPLYFFA treatment and were not associated with changes in glomerular function. The increases in serum creatinine may be due to inhibition of renal tubular secretion transporters [see Drug Interactions (7) and Clinical Pharmacology (12.2, 12.3)].

During MIPLYFFA treatment, use alternative measures that are not based on creatinine to assess renal function such as BUN, cystatin C, or measured GFR. Increases in creatinine reversed upon MIPLYFFA discontinuation [see Clinical Pharmacology (12.2)] .

6 ADVERSE REACTIONS

The following clinically significant adverse reactions are described below and elsewhere in the labeling:

- Hypersensitivity Reactions [see Warning and Precautions (5.1)].
- Increased Creatinine without Affecting Glomerular Function [see Warnings and Precautions (5.3)].

6.1 Clinical Trials Experience

Because clinical trials are conducted under widely varying conditions, adverse reaction rates observed in the clinical trials of a drug cannot be directly compared to rates in the clinical trials of another drug and may not reflect the rates observed in practice.

The safety of MIPLYFFA was evaluated in a randomized, double-blind, placebo-controlled, 12-month trial (Trial 1), which included 50 patients 2 to 19 years old with NPC [see Clinical Studies (14)] . Patients received weight-adjusted doses of MIPLYFFA (31 to 124 mg orally three times daily); 28 of the patients were exposed to MIPLYFFA for one year. In Trial 1, 78% of patients received miglustat. Forty-one out of 50 patients that were enrolled in Trial 1 continued into an open-label extension trial, which included 39 patients treated with MIPLYFFA for more than 1 year, 34 patients treated with MIPLYFFA for more than 2 years, and 17 patients treated with MIPLYFFA for more than 5 years.

The most common adverse reactions in Trial 1 (≥ 15%) in MIPLYFFA-treated patients who also received miglustat were upper respiratory tract infection, diarrhea, and decreased weight. Three (6%) of the MIPLYFFA-treated patients had the following adverse reactions that led to withdrawal from Trial 1: increased serum creatinine (one patient), and progressive urticaria and angioedema (two patients). Serious adverse reactions reported in MIPLYFFA-treated patients in Trial 1 were hypersensitivity reactions including urticaria and angioedema.

Table 1shows common adverse reactions in Trial 1 that occurred in at least 8% of MIPLYFFA-treated patients who also received miglustat.

Table 1: Adverse Reactions in ≥ 8% of Patients with NPC Treated with MIPLYFFA in Trial 1 (Subgroup Who Also Received Miglustat)
Adverse Reaction | MIPLYFFA with miglustat N=26 n (%) | Placebo with miglustat N=13 n (%)
Upper Respiratory Tract Infection* | 8 (31) | 2 (15)
Diarrhea | 6 (23) | 3 (23)
Decreased Weight | 4 (15) | 0
Decreased appetite | 3 (12) | 0
Tremor | 3 (12) | 0
Urticaria** | 3 (12) | 0
Headache | 3 (12) | 1 (8)
Lower respiratory tract infection | 3 (12) | 1 (8)
Seizure | 3 (12) | 1 (8)
* Upper Respiratory Tract Infection: Combined incidence of upper respiratory tract infection and rhinitis.
** Urticaria: Includes one patient in which urticaria occurred alone (3%) and two patients who had urticaria with angioedema (6%)

Decreased Weight

Adverse reactions of decreased weight were observed in four patients, who were also receiving concomitant miglustat during the trial. The decrease in weight resolved in all but one of the patients. The mean duration of the weight decrease was 33 days and ranged from 22 to 60 days. One patient had two separate instances of weight loss during the trial, lasting 22 and 24 days respectively. The mean weight loss was approximately 6% from baseline in all patients and MIPLYFFA administration was not interrupted in any patient.

Laboratory Findings

Thrombocytopenia:Thrombocytopenia was observed in three patients during the trial, all of whom were receiving miglustat for six months or longer at the time of enrollment. In two of these patients, the thrombocytopenia was present at baseline and persisted throughout the trial. In the other patient, the thrombocytopenia developed and resolved during the trial.

Increased Creatinine:Across clinical trials in patients with NPC, healthy subjects, and patients with other diseases, increases in serum creatinine (mean increase was 10-20%) occurred mainly within the first month of dosing and were reversible upon treatment discontinuation.

7 DRUG INTERACTIONS

7.1 Effect of MIPLYFFA on Other Drugs

Arimoclomol is an inhibitor of the organic cationic transporter 2 (OCT2) transporter and may increase the exposure of drugs that are OCT2 substrates [see Clinical Pharmacology (12.3)] . When MIPLYFFA is used concomitantly with OCT2 substrates, monitor for adverse reactions and reduce the dosage of the OCT2 substrate.

8 USE IN SPECIFIC POPULATIONS

8.1 Pregnancy

Risk Summary

Based on findings from animal reproduction studies, MIPLYFFA may cause embryofetal harm when administered during pregnancy. There are no available data on MIPLYFFA use in pregnant females to evaluate a drug-associated risk of major birth defects, miscarriage, or other adverse maternal or fetal outcomes. Advise pregnant females of the potential risk to the fetus.

In animal reproduction studies, oral administration of arimoclomol to pregnant rats and rabbits during organogenesis resulted in post-implantation loss and structural abnormalities in offspring. These occurred at exposures equal to or greater than 10- and 5-fold, in rats and rabbits respectively, the human exposure at the maximum recommended human daily dose of 372 mg (see Data).

The background risk of major birth defects and miscarriage for the indicated population is unknown. All pregnancies have a background risk of birth defect, loss, or other adverse outcomes. In the U.S. general population, the estimated background risk of major birth defects and miscarriage in clinically recognized pregnancies is 2% to 4% and 15% to 20%, respectively.

Data

Animal Data:In an embryofetal development study in pregnant rats, once daily oral doses of arimoclomol were administered throughout organogenesis from gestation day 6 to 17. Increased post-implantation loss was observed at 10-fold the human exposure, based on AUC at the MRHDD, together with increased ossification in the vertebrae and dilated brain ventricles in litters of dams dosed at equal to or greater than 8-fold the human exposure at the MRHDD.

In another embryofetal development study in pregnant rats in which arimoclomol was administered three times-daily throughout organogenesis from gestation day 6 to 17, there was an increase in postimplantation loss and reduced maternal, placental, and fetal weights at 14-fold the human exposure, based on AUC at the MRHD. In addition, fetuses of dams treated at this exposure level exhibited domed craniums, partially split sternum, hydrocephaly, dilated brain ventricles, dilated interventricular foramen, misaligned and misshapen hemicentres and misaligned ossification sites in the sternebrae, misaligned costal cartilage, increased ossification, cerebral and cerebellar hemorrhages, bipartite supraoccipital, large interparietal bone, marked enlargement of the anterior and posterior fontanelles, hyoid bone, meningocele and fusion of the jugal and maxilla.

In an embryofetal development study in pregnant rabbits, arimoclomol was administered once daily by oral gavage throughout organogenesis from gestation day 7 to 19. Increased incidences of minor skeletal variations (bent hyoid and unossified phalanx) were observed at 5-fold the human AUC at the MRHDD, coinciding with an adverse reduction of maternal body weight.

In a pre- and postnatal development study in pregnant rats, oral arimoclomol was administered from gestation day 6 to lactation day 21. Increased embryofetal lethality and reduced pup weight, with a slight reduction in maternal body weight gain, were observed at 10-fold the human AUC at the MRHDD.

8.2 Lactation

Risk Summary

There are no data on the presence of arimoclomol in human or animal milk, the effects on the breastfed infant, or the effects on milk production. The developmental and health benefits of breastfeeding should be considered along with the mother's clinical need for MIPLYFFA and any potential adverse effects on the breastfed infant from MIPLYFFA or from the underlying maternal condition.

8.3 Females and Males of Reproductive Potential

MIPLYFFA may cause embryofetal harm when administered to a pregnant female [see Use in Specific Populations (8.1)] .

Contraception

Females:Consider pregnancy planning and prevention for females of reproductive potential.

Infertility

Based on findings from animal studies, MIPLYFFA may impair fertility in females and males of reproductive potential. In a rat fertility study, oral administration of arimoclomol resulted in decreased male and female fertility at 9-fold and increased pre-implantation loss at 5-fold the human exposure, based on AUC at MRHD. It is not known if these effects are reversible [see Nonclinical Toxicology (13.1)] .

8.4 Pediatric Use

The safety and effectiveness of MIPLYFFA in combination with miglustat for the treatment of neurological manifestations of NPC have been established in pediatric patients 2 years of age and older. Use of MIPLYFFA in combination with miglustat for this indication is supported by evidence from a randomized, double-blind, placebo-controlled 12-month trial (Trial 1) [see Clinical Studies (14)].

The safety and effectiveness of MIPLYFFA have not been established in pediatric patients younger than 2 years of age.

Juvenile Animal Toxicity Data

In juvenile toxicity studies in rats, increased incidences of renal pelvic dilatation were observed at all dose levels corresponding to 4-, 7- and 17-fold the human exposure based on AUC at MRHDD after both 2 and 8 weeks of dosing when animals were dosed from postnatal day 7.

8.5 Geriatric Use

NPC is largely a disease of pediatric and young adult patients. Clinical trials of MIPLYFFA in combination with miglustat in patients with NPC did not include patients aged 65 years or older.

8.6 Renal Impairment

The recommended MIPLYFFA dosage in combination with miglustat in patients with an eGFR 15 mL/minute to < 50 mL/minute is lower than the recommended dosage (less frequent dosing) in patients with normal renal function [see Dosage and Administration (2.2)]. The recommended dosage of MIPLYFFA in combination with miglustat in patients with an eGFR ≥ 50 mL/minute is the same as the recommended dosage in patients with normal renal function.

Plasma concentrations of arimoclomol increased in patients with eGFR ≥ 15 mL/minute to < 50 mL/minute [see Clinical Pharmacology (12.3)].

The pharmacokinetics of arimoclomol have not been evaluated in patients with eGFR < 15 mL/minute.

11 DESCRIPTION

MIPLYFFA capsules contain arimoclomol citrate. Arimoclomol citrate is a crystalline powder of white to off-white color that is freely soluble in water. The chemical name is N-[(2R, Z)-2-hydroxy-3-(1piperidyl)propoxy]pyridine-3-carboximidoyl chloride, 1-oxide, citrate.

The empirical formula is C20H28ClN3O10and the molecular weight is 505.90 g/mol. The chemical structure is:

MYPLIFFA contains 47 mg, 62 mg, 93 mg, or 124 mg of arimoclomol (equivalent to 75 mg, 100 mg, 150 mg, or 200 mg of arimoclomol citrate). The inactive ingredients are microcrystalline cellulose (MCC) and magnesium stearate. The inactive ingredients are not water soluble and will remain undissolved if the contents of the capsule are added to beverages or soft food [see Dosage and Administration (2.3)].

The capsule shells contain hypromellose, titanium dioxide, and one or more of the following: Brilliant Blue FCF-FD&C Blue 1, Yellow iron oxide and Red iron oxide.

12 CLINICAL PHARMACOLOGY

12.1 Mechanism of Action

The mechanism(s) by which arimoclomol exerts its clinical effects in patients with NPC is unknown.

12.2 Pharmacodynamics

The effect of arimoclomol (744 mg/day for 28 days) on serum creatinine was assessed in 16 healthy male subjects. A reversible increase in mean serum creatinine of 19% was observed after 21 days of treatment. No effect on glomerular function (GFR,^125I-iothalamate clearance) or renal hemodynamics (effective renal plasma flow (ERPF);^131I-hippuran clearance) was observed [see Warnings and Precautions (5.3), Adverse Reactions (6.1), and Drug Interactions (7)].

Cardiac Electrophysiology

The effect of arimoclomol 124 mg and 372 mg (3 times the maximum recommended dosage) administered three times a day (372 mg/day and 1116 mg/day) on ECG was evaluated in a randomized, partially double-blind, placebo-, and positive-controlled (moxifloxacin 400 mg), multipledose, 4-way crossover trial in 34 healthy male subjects. In this trial, arimoclomol did not prolong the QTc interval to a clinically relevant extent.

12.3 Pharmacokinetics

Arimoclomol exhibited linear and dose proportional pharmacokinetics following oral administration of doses ranging from 62 to 372 mg (three times the maximum recommended dosage) three times a day in healthy subjects. The plasma Cmaxand AUC0-8hrof arimoclomol at the 248 mg dose (two times the maximum recommended dosage) are summarized in Table 2.

Table 2: Geometric mean (CV%) Pharmacokinetic Parameters of Arimoclomol Following Oral Administration in Healthy Subjects
Plasma PK Parameters | 248 mg arimoclomol oral administration three times a day
Plasma PK Parameters | Day 1 (first dose) | Day 6 (steady state)
AUC0-8hr(hr·ng/mL) | 5317 (17%) | 7207 (19%)
Cmax(ng/mL) | 1749 (49%) | 2090 (23%)

Absorption

The absolute bioavailability of arimoclomol following oral administration has not been determined. The median time to reach maximum plasma arimoclomol concentration (tmax) was approximately 0.5 hours.

Effect of Food

No clinically significant difference in arimoclomol pharmacokinetics were observed following administration of a high-fat meal (1000 calories, 60% fat) to healthy subjects.

Distribution

The mean apparent volume of distribution (VZ/F) of arimoclomol at steady state in healthy adult subjects is 211 L. A dose-dependent increase in arimoclomol cerebral spinal fluid concentrations was seen at steady state. Plasma protein binding of arimoclomol is approximately 10%.

Elimination

The elimination half-life of arimoclomol is approximately 4 hours. The mean apparent clearance of arimoclomol (CL/F) at steady state is 34 L/hr in healthy adult subjects.

Metabolism:Arimoclomol is predominantly metabolized through glutathionation, O-glucuronidation and NO-oxime cleavage.

Excretion:Following a single dose of radiolabeled arimoclomol 100 mg to healthy male subjects under fasted conditions, approximately 12% of the dose was recovered in feces and 77.5% in urine (42% unchanged).

Drug Interaction Studies

In Vitro Studies:Cytochrome P450 (CYP) Enzymes: Arimoclomol is not an inhibitor or inducer of CYP1A2, CYP2B6, CYP2C8, CYP2C9, CYP2C19, CYP2D6 or CYP3A4/5.

Transporter Systems:Arimoclomol is an inhibitor of OCT2 and may cause relevant changes in exposure of OCT2 substrates including the endogenous substrate creatinine [see Drug Interactions (7.1)]. Arimoclomol is not an inhibitor of P-gp, BCRP, OATP1B1, OATP1B3, OAT1, OAT3, MATE1 and MATE2-K transporters. Arimoclomol is a substrate of MATE1 and MATE2-K transporters; MATE1 and MATE2-K inhibitors are not expected to have a clinically relevant effect on arimoclomol exposure.

Specific Populations

Pediatric Patients:In pediatric NPC patients who received the recommended dosing regimens, the estimated steady state mean ± SD serum Ctroughand Cmaxarimoclomol concentrations are 206 ± 60 and 523 ± 194 ng/mL, respectively.

Patients with Renal Impairment:In a renal impairment study, subjects with moderate to severe renal impairment (estimated glomerular filtration rate [eGFR] 15-49 mL/minute) had an approximately 2-fold increase in total exposure to arimoclomol (AUCinf) compared to subjects with normal renal function (eGFR ≥ 90 mL/minute) [see Dosage and Administration (2.2)] . There was no clinically meaningful difference in exposure to arimoclomol in subjects with an eGFR of ≥ 50 mL/minute. MIPLYFFA was not evaluated in patients with eGFR < 15 mL/minute.

Patients with Hepatic Impairment:No clinically relevant differences in arimoclomol pharmacokinetics were observed in patients with mild to moderate hepatic impairment (Child-Pugh Score A or B) compared to subjects with normal hepatic function. MIPLYFFA has not been studied in patients with severe hepatic impairment (Child-Pugh Criteria C).

13 NONCLINICAL TOXICOLOGY

13.1 Carcinogenesis, Mutagenesis, Impairment of Fertility

Carcinogenesis

In a 2-year carcinogenicity study in Han Wistar rats, and a 26-week carcinogenicity study in Transgenic rasH2 mice, oral administration of arimoclomol did not increase the incidence of tumors at systemic exposures that were approximately 8-fold and 11-fold the human exposure, based on AUC at the MRHD.

Mutagenesis

Arimoclomol was not mutagenic or clastogenic in a standard battery of genotoxicity tests (bacterial mutagenicity [Ames], chromosomal aberration in Chinese Hamster Ovary cells, mouse lymphoma forward mutation, mouse and rat bone marrow micronucleus).

Impairment of Fertility

In a fertility and early embryonic development study in rats, once daily oral arimoclomol doses were administered to males for 4 weeks prior to and throughout mating (for a total of 10 weeks) and to females for 2 weeks prior to mating and to gestation day 6. A reduction in fertility and fecundity indices was noted for both sexes at 9-fold the human exposure, based on AUC at the MRHD. At the same dose level, a reduction in the number of corpora lutea was observed in females, and reduced sperm motility, immotile sperm, reduced sperm count and increased sperm abnormalities were observed in males. A dose-dependent increase in preimplantation loss was noted across all treated groups (equal to or greater than 5-fold the human exposure, based on AUC at the MRHD), which resulted in a reduction in the number of live embryos [see Use in Specific Populations (8.3)].

14 CLINICAL STUDIES

Safety and effectiveness of MIPLYFFA were assessed in Trial 1, a randomized, double-blind, placebocontrolled, 12-month trial in patients 2 to 19 years of age who had a molecularly confirmed diagnosis of NPC (NCT02612129). Fifty patients were randomized 2:1 to treatment with weight-adjusted MIPLYFFA (31 to 124 mg) or placebo orally three times per day. The randomization was stratified by miglustat use status at baseline.

Efficacy assessments, including the rescored 4-domain NPC Clinical Severity Scale (R4DNPCCSS) score, were performed at baseline and every 3 months until 12 months of treatment. The R4DNPCCSS is a measure of NPC disease progression that consists of the four items assessing ambulation, speech, swallow, and fine motor skills that patients with NPC and their caregivers and physicians have identified as most relevant with higher scores representing greater severity of disease.

In Trial 1, 76% and 81% of patients in the MIPLYFFA and placebo groups, respectively, received miglustat six months or longer prior to the time of enrollment. For the subgroup of patients who also received miglustat at enrollment, the mean age was 11.6 years, the mean time since first NPC symptom was 8.5 years, and the mean age at onset of first neurological symptom was 4.9 years. In this subgroup, 56% of patients were females, 87% were white, 5% were Asian, 3% were native Hawaiian or other Pacific Islander, and 5% were unknown. The mean baseline R4DNPCCSS score was higher in the MIPLYFFA group (n=26; mean=8.9) than the placebo group (n=13; mean=7), with an overall mean R4DNPCCSS score of 8.3.

In the MIPLYFFA group, four patients discontinued the study: one patient due to consent withdrawal and three patients due to adverse reactions [see Adverse Reactions (6.1)]. In the placebo group, one patient discontinued the study due to an adverse event.

Table 3displays the change from baseline in R4DNPCCSS score at month 12 in patients 2 to

19 years of age with NPC who also received miglustat in Trial 1. See Figure 1for the mean change in R4DNPCCSS score from baseline over time by treatment group in patients 2 to 19 years of age with NPC who also received miglustat.

Table 3: MIPLYFFA and Placebo Change from Baseline in R4DNPCCSS Score at Month 12 in Patients 2 to 19 Years of Age with NPC (Subgroup Who Also Received Miglustat) (Trial 1)
 | R4DNPCCSS Score
 | Baseline |  | Change from Baseline to Month 12
 | MIPLYFFA with miglustat (N=26) | Placebo with miglustat (N=13) | MIPLYFFA with miglustat (N=22) | Placebo with miglustat (N=12)
Mean (SD) | 8.9 (6.1) | 7 (5.8) | -0.2 (1) | 1.9 (3.4)
Median | 7.5 | 5 | 0 | 1
LS Mean (SE) |  |  | -0.2 (0.5) | 2 (0.7)
Placebo-subtracted Difference (95% CI)[1] |  |  | -2.2 (-3.8, -0.6)
[1]Changes in R4DNPCCSS score from baseline to month 12 were compared using an analysis of variance (ANCOVA) model fitted with treatment and baseline R4DNPCCSS score as covariate.

Figure 1: MIPLYFFA and Placebo Mean Change from Baseline (± SE) in R4DNPCCSS Score Over Time in Patients 2 to 19 Years of Age with NPC Who Also Received Miglustat (Trial 1)

There were insufficient data to determine the effectiveness of the use of MIPLYFFA without miglustat for the treatment of neurological manifestations in patients with NPC.

16 HOW SUPPLIED/STORAGE AND HANDLING

How Supplied

MIPLYFFA (arimoclomol) capsules are supplied in high-density polyethylene (HDPE) bottles with child-resistant closure as follows:

MIPLYFFA Strength | Capsules Description | Package Configuration | NDC No.
47 mg | White opaque body with black printing “47”, and green opaque cap with black printing “OZ” | Bottle of 90 capsules | 72542-147-01
62 mg | White opaque body with black printing “62”, and yellow opaque cap with black printing “OZ”. | Bottle of 90 capsules | 72542-162-01
93 mg | White opaque body with black printing “93”, and orange opaque cap with black printing “OZ” | Bottle of 90 capsules | 72542-193-01
124 mg | White opaque body with black printing “124”, and red opaque cap with black printing “OZ” | Bottle of 90 capsules | 72542-124-01

Storage and Handling

Store MIPLYFFA at 20°C to 25°C (68°F to 77°F); excursions permitted between 15°C to 30°C (59°F to 86°F) [see USP Controlled Room Temperature]. Store in original container. Protect from light.

17 PATIENT COUNSELING INFORMATION

Advise the patient and/or caregiver to read the FDA-approved patient labeling (Instructions for Use).

Drug Interactions

Advise the patient to inform his/her healthcare provider if he/she is taking, or plan to take, any prescription or over-the-counter medications and supplements because of the potential for drug interactions [see Drug Interactions (7) and Clinical Pharmacology (12.3)].

Hypersensitivity Reactions

Advise the patient or caregiver to contact his/her healthcare provider immediately if urticaria (hives), shortness of breath, persistent cough, or facial swelling develop in response to MIPLYFFA treatment [see Warnings and Precautions (5.1)].

Embryofetal Toxicity

MYPLIFFA may cause embryo-fetal harm. Advise the pregnant female of the potential risk to the fetus. Advise a female of reproductive potential and caregiver to inform their healthcare provider of a known or suspected pregnancy [see Warnings and Precautions (5.1) and Use in Specific Populations (8.1)] . Counsel females of reproductive potential about pregnancy planning and prevention [see Use in Specific Populations (8.3)].

Infertility

Advise the female and male of reproductive potential that MIPLYFFA may impair fertility [see Use in Specific Populations (8.1, 8.3)].

Manufactured by:
Zevra Denmark A/S
2000 Frederiksberg, Denmark

Manufactured for:
Zevra Therapeutics, Inc.
Celebration, FL 34747, USA
© 2024 Zevra Therapeutics, Inc. All rights reserved.
U.S. Patent Nos. 9,289,472, 9,884,058 and 11,045,460. MIPLYFFA is a trademark of Zevra Therapeutics, Inc.

INSTRUCTIONS FOR USE

MIPLYFFA™ [mye plye' fah]

(arimoclomol) capsules for oral use

This Instructions for Use contains information on how to take or give MIPLYFFA. Read this Instructions for Use before taking or giving MIPLYFFA and each time you get a refill. There may be new information. This Instructions for Use does not take the place of talking to your or your child's healthcare provider about your or your child's medical condition or treatment.

Important Information You Need to Know Before Taking or Giving MIPLYFFA

- Take or give MIPLYFFA capsules exactly as instructed by your healthcare provider.
- Your healthcare provider will tell you the number of MIPLYFFA capsules to take or give for the prescribed dose.
- MIPLYFFA capsules can be swallowed whole with or without food.
- If you or your child have difficulty swallowing capsules, MIPLYFFA capsules can be opened and:
  - can be taken or given by mouth (see Step 1 to Step 5) or
  - through a feeding tube (see Step 6 to 13).
- If you miss a dose of MIPLYFFA, skip the missed dose and take or give the next dose of MIPLYFFA at your regularly scheduled time.

Preparing to take or give MIPLYFFA by mouth if you have difficulty swallowing capsules

Supplies needed to take or give 1 dose of MIPLYFFA:

- 1 MIPLYFFA capsule,
- 15 mL of liquid (water or apple juice) or soft food (apple sauce, yogurt, or pudding).
- small cup
- spoon

Step 1:
Add 15 mL of water, apple juice, apple sauce, yogurt, or pudding into a small cup.
Adding MIPLYFFA to any other liquids is not recommended.

Step 2:
Carefully open 1 MIPLYFFA capsule by twisting the top and bottom of the capsule (see Figure A). Sprinkle the entire contents of the capsule into the small cup (see Figure B).

Step 3:
Stir the mixture for 15 seconds with a spoon (see Figure C).

- After mixing, some of the capsule contents may remain in the mixture.

Step 4:
Swallow all of the mixture right away (see Figure D).
Do notsave any of the mixture for later use.
Throw away the MIPLYFFA mixture if not swallowed right away.

Step 5:
Throw away the empty MIPLYFFA capsule shells in the household trash.

Preparing to take or give MIPLYFFA through a feeding tube (nasogastric or gastric tube)

Supplies needed to take 1 dose of MIPLYFFA:

- 1 MIPLYFFA capsule
- 1 feeding tube syringe (at least 20 mL)
- water
- small cup
- spoon

Step 6:
Use the feeding tube syringe to measure 20 mL of water into a small cup (see Figure E).

Step 7:
Carefully open 1 MIPLYFFA capsule by twisting the top and bottom of capsule (see Figure F). Sprinkle the entire contents of the capsule into the small cup (see Figure G).
Do notadd the contents of the capsule to any other liquids besides water.

Step 8:
Stir the mixture for 15 seconds with a spoon (see Figure H).

- After mixing, some of the capsule contents may remain in the mixture.

Step 9:
Place the feeding tube syringe in the mixture. Pull up on the feeding tube syringe plunger (indicated with a “ P” on the figure) to withdraw the whole mixture into the feeding tube syringe (see Figure I).

Step 10:
Attach the feeding tube syringe to the feeding tube. Slowly push the plunger (P) to give or take the mixture right away through the feeding tube (see Figure J).
Do notsave any of the mixture for later use.
Throw away the MIPLYFFA mixture if not given or taken right away.

Step 11:
Disconnect the empty feeding tube syringe from the feeding tube.
Fill the small cup with water.

Step 12:
Fill the syringe with 5 mL of water and slowly push the plunger (P) to flush the feeding tube with water (see Figure K).

Step 13:
Throw away the empty MIPLYFFA capsule shells in the household trash.

Storing MIPLYFFA

- Store MIPLYFFA at room temperature between 68°F to 77°F (20°C to 25°C).
- Store in original container. Protect from light.

Manufactured for:
Zevra Therapeutics Inc.
Celebration FL, USA
© 2024 Zevra Therapeutics, Inc. All rights reserved.
MIPLYFFA is a trademark of Zevra Therapeutics, Inc.

This Instructions for Use has been approved by the U.S. Food and Drug Administration Issued: September/2024

Principal Display Panel – 47 mg Carton Label

NDC 72542-147-01

Rx Only

MIPLYFFA™

(arimoclomol) capsules

47 mg

90 capsules

For Oral Use

Principal Display Panel – 62 mg Carton Label

NDC 72542-162-01

Rx Only

MIPLYFFA™

(arimoclomol) capsules

62 mg

90 capsules

For Oral Use

Principal Display Panel – 93 mg Carton Label

NDC 72542-193-01

Rx Only

MIPLYFFA™

(arimoclomol) capsules

93 mg

90 capsules

For Oral Use

Principal Display Panel – 124 mg Carton Label

NDC 72542-124-01

Rx Only

MIPLYFFA™

(arimoclomol) capsules

124 mg

90 capsules

For Oral Use